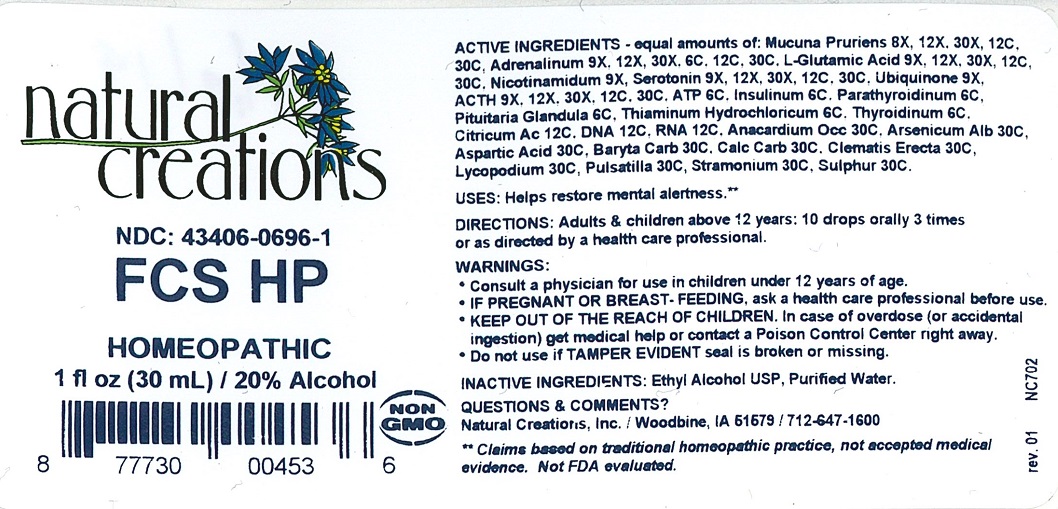 DRUG LABEL: FCS HP
NDC: 43406-0696 | Form: LIQUID
Manufacturer: Natural Creations, Inc.
Category: homeopathic | Type: HUMAN OTC DRUG LABEL
Date: 20251210

ACTIVE INGREDIENTS: EPINEPHRINE 30 [hp_C]/1 mL; GLUTAMIC ACID 30 [hp_C]/1 mL; MUCUNA PRURIENS SEED 30 [hp_C]/1 mL; NIACINAMIDE 9 [hp_X]/1 mL; SEROTONIN 30 [hp_C]/1 mL; UBIDECARENONE 9 [hp_X]/1 mL; CORTICOTROPIN 30 [hp_C]/1 mL; ADENOSINE TRIPHOSPHATE 6 [hp_C]/1 mL; INSULIN PORK 6 [hp_C]/1 mL; SUS SCROFA PARATHYROID GLAND 6 [hp_C]/1 mL; SUS SCROFA PITUITARY GLAND 6 [hp_C]/1 mL; THIAMINE HYDROCHLORIDE 6 [hp_C]/1 mL; THYROID, UNSPECIFIED 6 [hp_C]/1 mL; ANHYDROUS CITRIC ACID 12 [hp_C]/1 mL; HERRING SPERM DNA 12 [hp_C]/1 mL; SACCHAROMYCES CEREVISIAE RNA 12 [hp_C]/1 mL; ANACARDIUM OCCIDENTALE FRUIT 30 [hp_C]/1 mL; ARSENIC TRIOXIDE 30 [hp_C]/1 mL; ASPARTIC ACID 30 [hp_C]/1 mL; BARIUM CARBONATE 30 [hp_C]/1 mL; OYSTER SHELL CALCIUM CARBONATE, CRUDE 30 [hp_C]/1 mL; CLEMATIS RECTA FLOWERING TOP 30 [hp_C]/1 mL; LYCOPODIUM CLAVATUM SPORE 30 [hp_C]/1 mL; ANEMONE PULSATILLA 30 [hp_C]/1 mL; DATURA STRAMONIUM 30 [hp_C]/1 mL; SULFUR 30 [hp_C]/1 mL
INACTIVE INGREDIENTS: ALCOHOL; WATER

FCS HP

ACTIVE INGREDIENT

ACTIVE INGREDIENTS - equal amounts of: Mucuna Pruriens 8X, 12X, 30X, 12C, 30C, Adrenalinum 9X, 12X, 30X, 6C, 12C, 30C, L-Glutamic Acid 9X, 12X, 30X, 12C, 30C, Nicotinamidum 9X, Serotonin 9X, 12X, 30X, 12C, 30C, Ubiquinone 9X, ACTH 9X, 12X, 30X, 12C, 30C, ATP 6C, Insulinum 6C, Parathyroidinum 6C, Pituitaria Glandula 6C, Thiaminum Hydrochloricum 6C, Thyroidinum 6C, Citricum Ac 12C, DNA 12C, RNA 12C, Anacardium Occ 30C, Arsenicum Alb 30C, Aspartic Acid 30C, Baryta Carb 30C, Calc Carb 30C, Clematis Erecta 30C, Lycopodium 30C, Pulsatilla 30C, Stramonium 30C, Sulphur 30C.

PURPOSE

Uses: Helps restore mental alertness.**

INDICATIONS AND USAGE

Uses: Helps restore mental alertness.**

DOSAGE AND ADMINISTRATION

Directions: Adults & children above 12 years: 10 drops orally 3 times daily, or as directed by a health care professional.

KEEP OUT OF REACH OF CHILDREN

KEEP OUT OF THE REACH OF CHILDREN. In case of overdose (or accidental ingestion) get medical help or contact a Poison Control Center right away.

WARNINGS:

- Consult a physician for use in children under 12 years of age.
- IF PREGNANT OR BREAST-FEEDING, ask a health care professional before use.
- KEEP OUT OF THE REACH OF CHILDREN. In case of overdose (or accidental ingestion) get medical help or contact a Poison Control Center right away.
- Do not use if TAMPER EVIDENT seal is broken or missing.

Inactive Ingredients: Ethyl Alcohol USP, Purified Water.

Questions & Comments?

Natural Creations, Inc. / Woodbine, IA 51579 / 712-647-1600

REFERENCES

** Claims based on traditional homeopathic practice, not accepted medical evidence. Not FDA evaluated.

PACKAGE LABEL

NDC: 43406–0696-1

FCS HP

HOMEOPATHIC

1 fl oz (30 mL) / 20% Alcohol

UPC: 877730004536